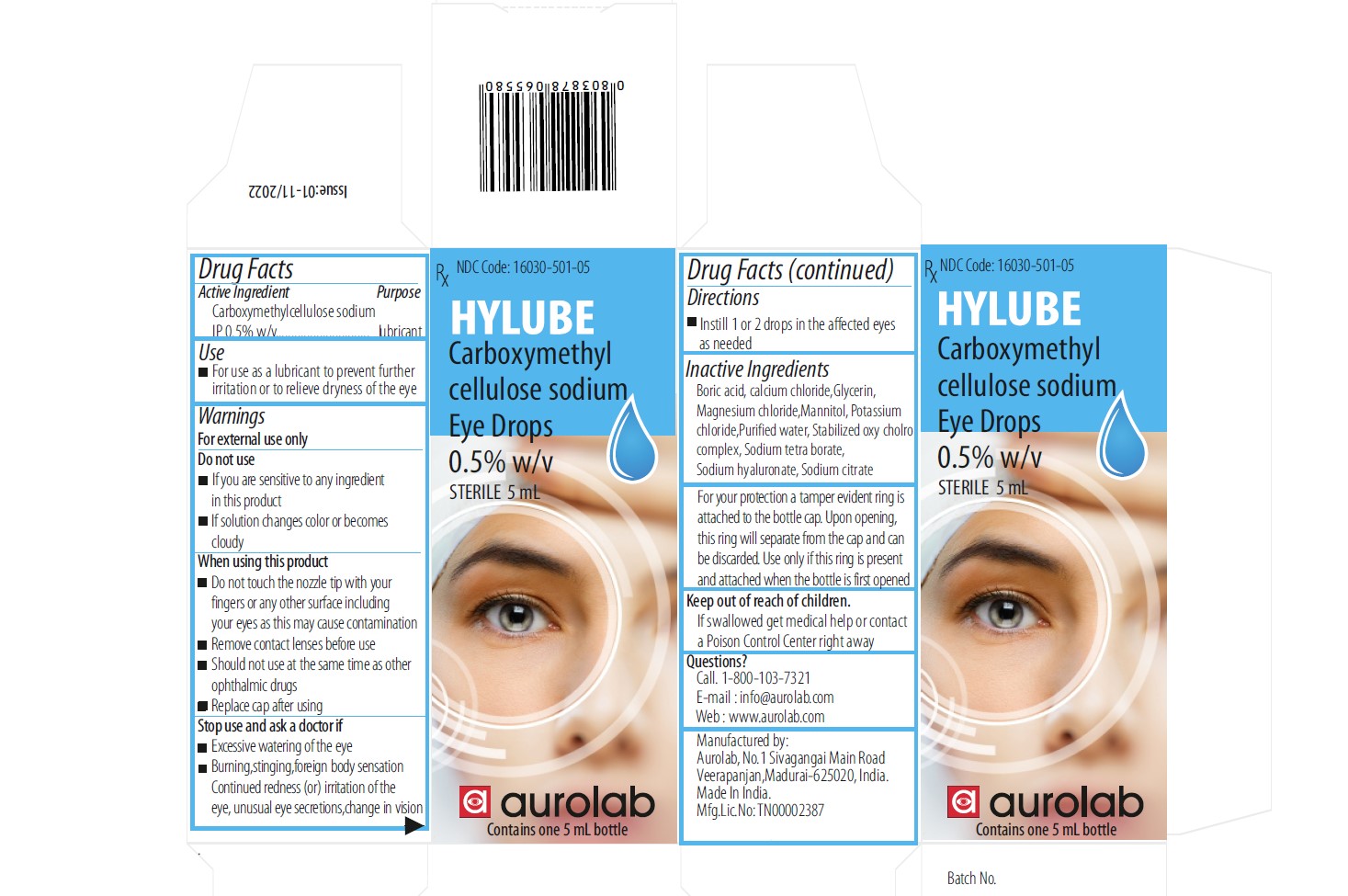 DRUG LABEL: Carboxymethylcellulose Sodium Eye Drops 0.5%
NDC: 16030-501 | Form: FOR SOLUTION
Manufacturer: Aurolab
Category: otc | Type: HUMAN OTC DRUG LABEL
Date: 20260127

ACTIVE INGREDIENTS: CARBOXYMETHYLCELLULOSE SODIUM, UNSPECIFIED 5 mg/1 mL
INACTIVE INGREDIENTS: WATER; BORIC ACID; SODIUM CHLORITE; CALCIUM CHLORIDE; MAGNESIUM CHLORIDE; POTASSIUM CHLORIDE; SODIUM CITRATE; MANNITOL; GLYCERIN; PEG-9 DIGLYCIDYL ETHER/SODIUM HYALURONATE CROSSPOLYMER; SODIUM BORATE

Active ingredient

Carboxymethyl cellulose sodium Eye Drops 0.5% w/v

DIRECTIONS FOR USE

- lnstill 1or 2 drops in the affected eye, as needed

INACTIVE INGREDIENT

1.Boric acid

2.Calcium chloride

3.Glycerin
4.Magnesium chloride

5.Mannitol

6.Potassium chloride

7.Purified water

8.Stablized oxy cholro complex

9.Sodium tetra borate
10.Sodium hyaluronate

11.Sodium citrate

Tamper Protection

- For your protection a tamper evident ring is attached to the bottlecap
- Upon opening, this will separate from the cap and can be discarded
- Use only if this ring is present and attached when the bottle is first opened

Use

For use as a lubricant to prevent further irritation or to relieve dryness of the eye

Questions

Call. 1-800-103-7321
E-mail : info@aurolab.com
Web : www.aurolab.com

Keep out of reach of children

If swallowed get medical help or contact a Poison Control Center right away

Stop use and ask a doctor if

1.Excessive watering of the eye

2.Burning, stinging,foreign body sensation Continued redness (or) irritation of the eye, unusual eye secretions, change in vision

Do not use

1.If you are sensitive to any ingredient in this product
2.If solution changes color or becomes cloudy

Warnings

For external use only

Indication & usage

Do not touch the nozzle tip to any surface since this may contaminate the solution
Remove contact lenses before use Should not use at the same time as other ophthalmic drugs
Replace cap after using

Dose

Instill 1 or 2 drops in the affected eyes as needed

Eye lubricant